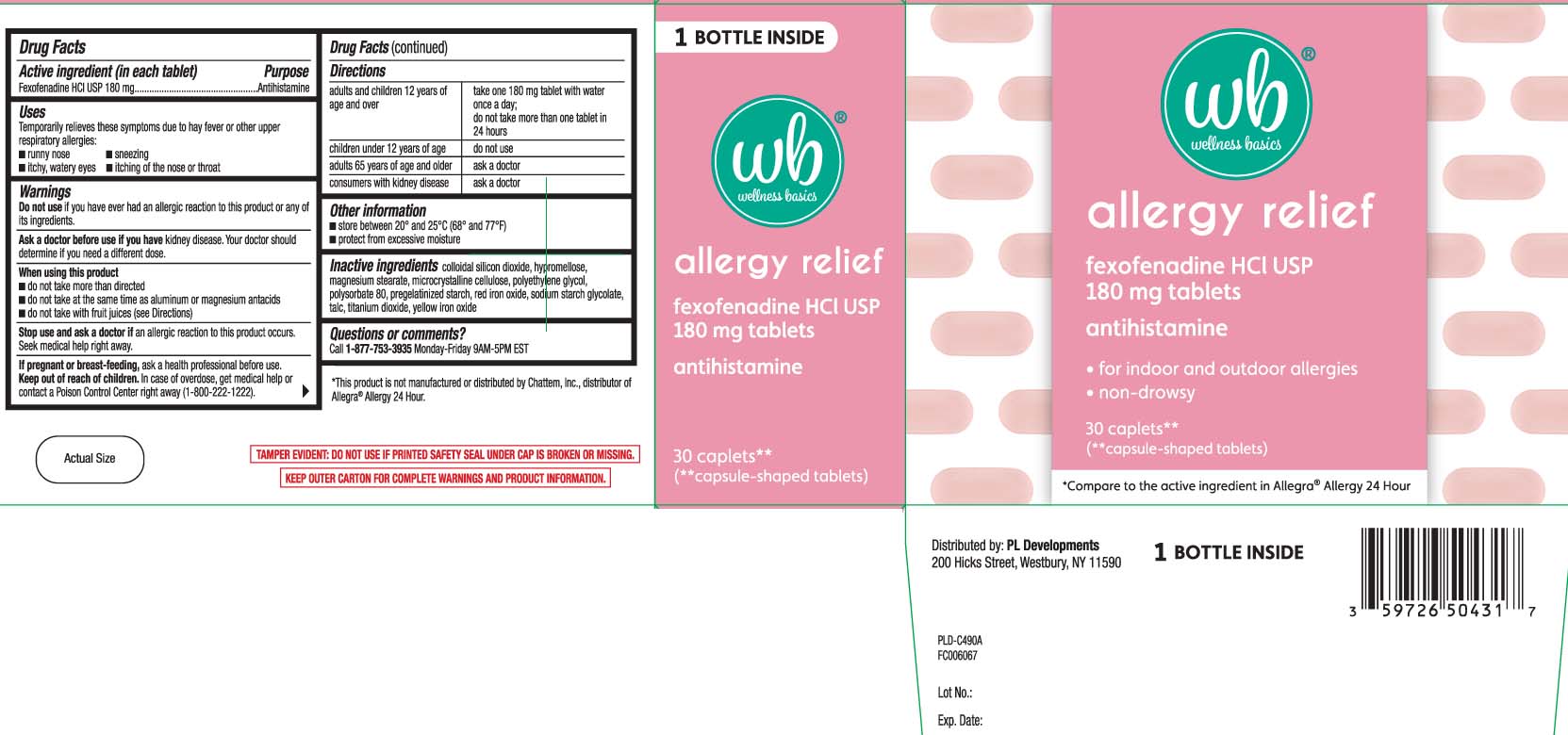 DRUG LABEL: Allergy Relief
NDC: 59726-564 | Form: TABLET, COATED
Manufacturer: P & L Development, LLC
Category: otc | Type: HUMAN OTC DRUG LABEL
Date: 20221213

ACTIVE INGREDIENTS: FEXOFENADINE HYDROCHLORIDE 180 mg/1 1
INACTIVE INGREDIENTS: SILICON DIOXIDE; HYPROMELLOSES; FERRIC OXIDE RED; FERRIC OXIDE YELLOW; MAGNESIUM STEARATE; POLYETHYLENE GLYCOL, UNSPECIFIED; TITANIUM DIOXIDE; MICROCRYSTALLINE CELLULOSE; STARCH, CORN; POLYSORBATE 80; SODIUM STARCH GLYCOLATE TYPE A CORN; TALC

DRUG FACTS

Active ingredient (in each tablet)

Fexofenadine HCL USP 180 mg

Purpose

Antihistamine

Uses

temporarily relieves these symptoms due to hay fever or other upper respiratory allergies:

- runny nose
- itchy, watery eyes
- sneezing
- itching of the nose or throat

Warnings

Do not use

if you have ever had an allergic reaction to this product or any of its ingredients.

Ask a doctor before use if you have

kidney disease. Your doctor should determine if you need a different dose.

When using this product

- do not take more than directed
- do not take at the same time as aluminum or magnesium antacids
- do not take with fruit juices (see Directions)

Stop use and ask a doctor if

an allergic reaction to this product occurs. Seek medical help right away.

If pregnant or breast-feeding,

ask a health professional before use.

Keep out of reach of children.

In case of overdose, get medical help or contact a Poison Control Center right away (1-800-222-1222).

Directions

adults and children 12 years of age and over | take one 180 mg tablet with water once a day; do not take more than 1 tablet in 24 hours
children under 12 years of age | do not use
adults 65 years of age and older | ask a doctor
consumers with kidney disease | ask a doctor

Other information

- safety sealed: do not use if printed safety seal under cap is missing or broken or if individual blisted units are torn or opened
- store between 20º and 25ºC (68º and 77ºF)
- protect from excessive moisture

Inactive ingredients

colloidal silicon dioxide, hypromellose, magnesium stearate, microcrystalline cellulose, polyethylene glycol, polysorbate 80, pregelatinized starch, red iron oxide, sodium starch glycolate, talc, titanium dioxide, yellow iron oxide

Questions or comments?

call 1-877-753-3935 Monday- Friday 9AM- 5PM EST

Principal Display Panel

allergy relief

Fexofenadine HCL USP 180 mg tablets

antihistamine

- for indoor and outdoor allergies
- non-drowsy

caplets**

(**capsule-shaped tablets)

*Compare to the active ingredient in Allegra® Allergy 24 Hour

*This product is not manufactured or distributed by Chattem Inc., distributor of Allegra® Allergy 24 hour.

TAMPER EVIDENT: DO NOT USE IF PRINTED SAFETY SEAL UNDER CAP IS BROKEN OR MISSING.

KEEP OUTER CARTON FOR COMPLETE WARNINGS AND PRODUCT INFORMATION.

Distributed by: PL Developments

200 Hicks Street Westbury, NY 11590

Product Label

WELLNESS BASICS Allergy Relief